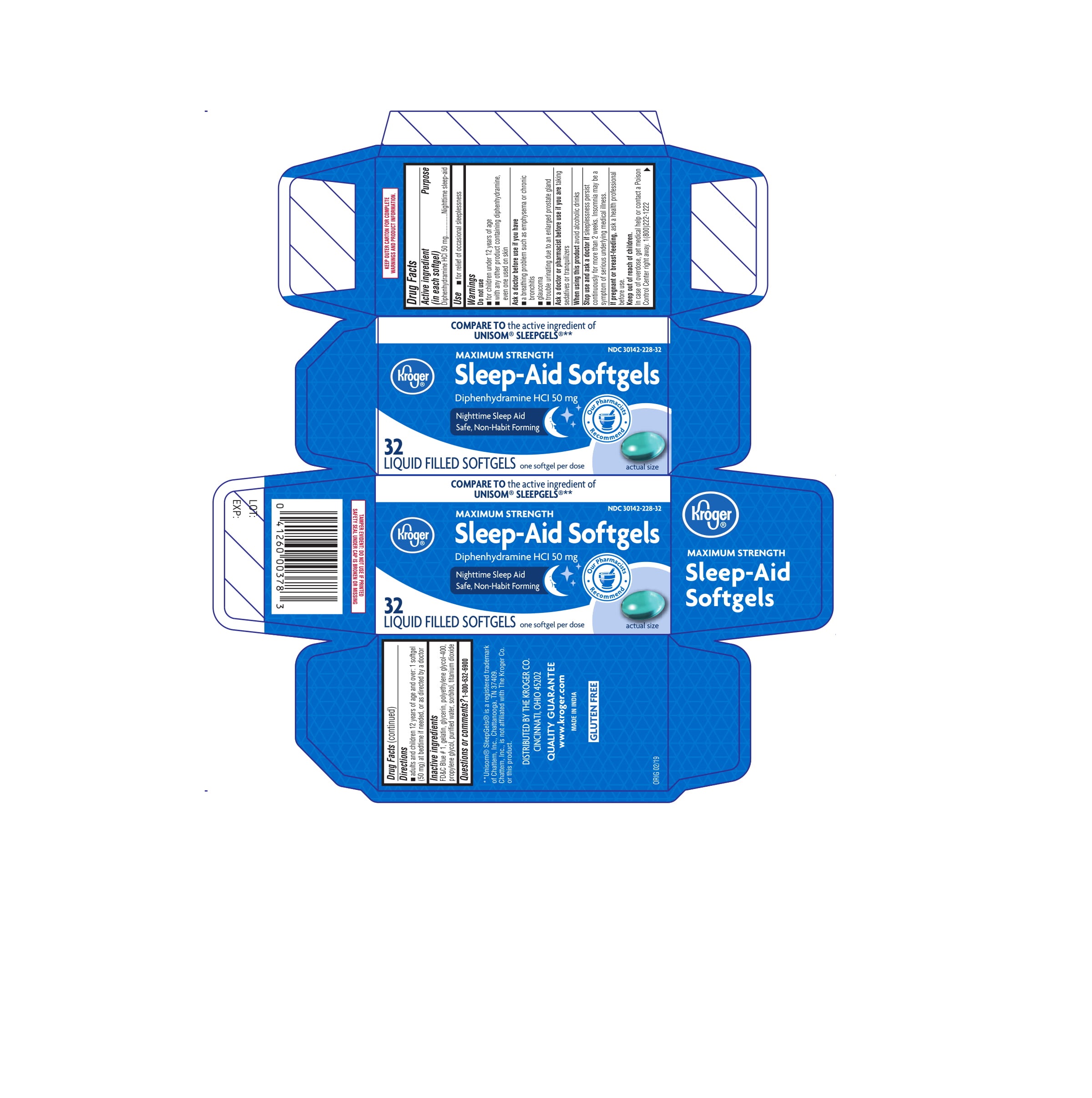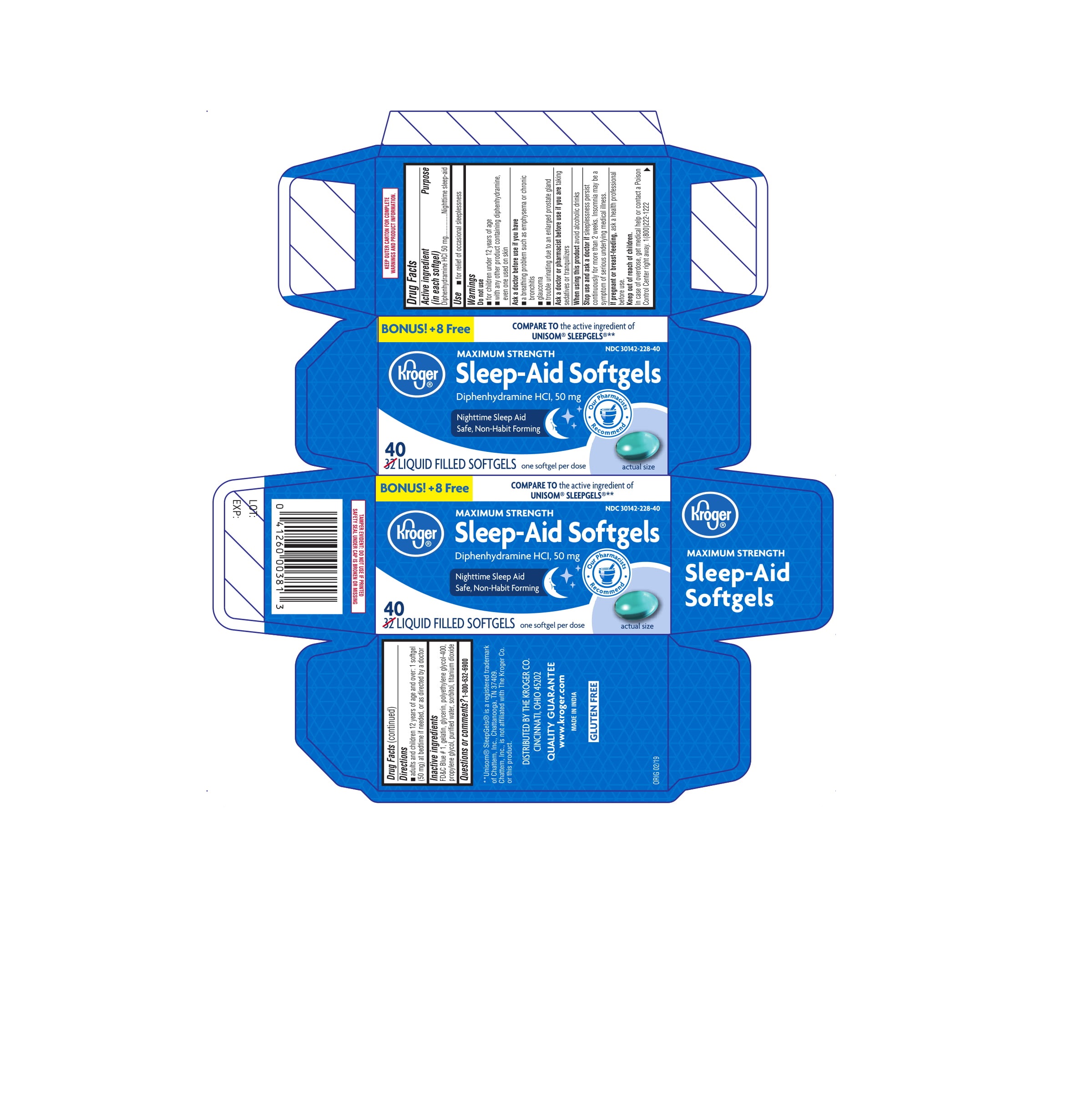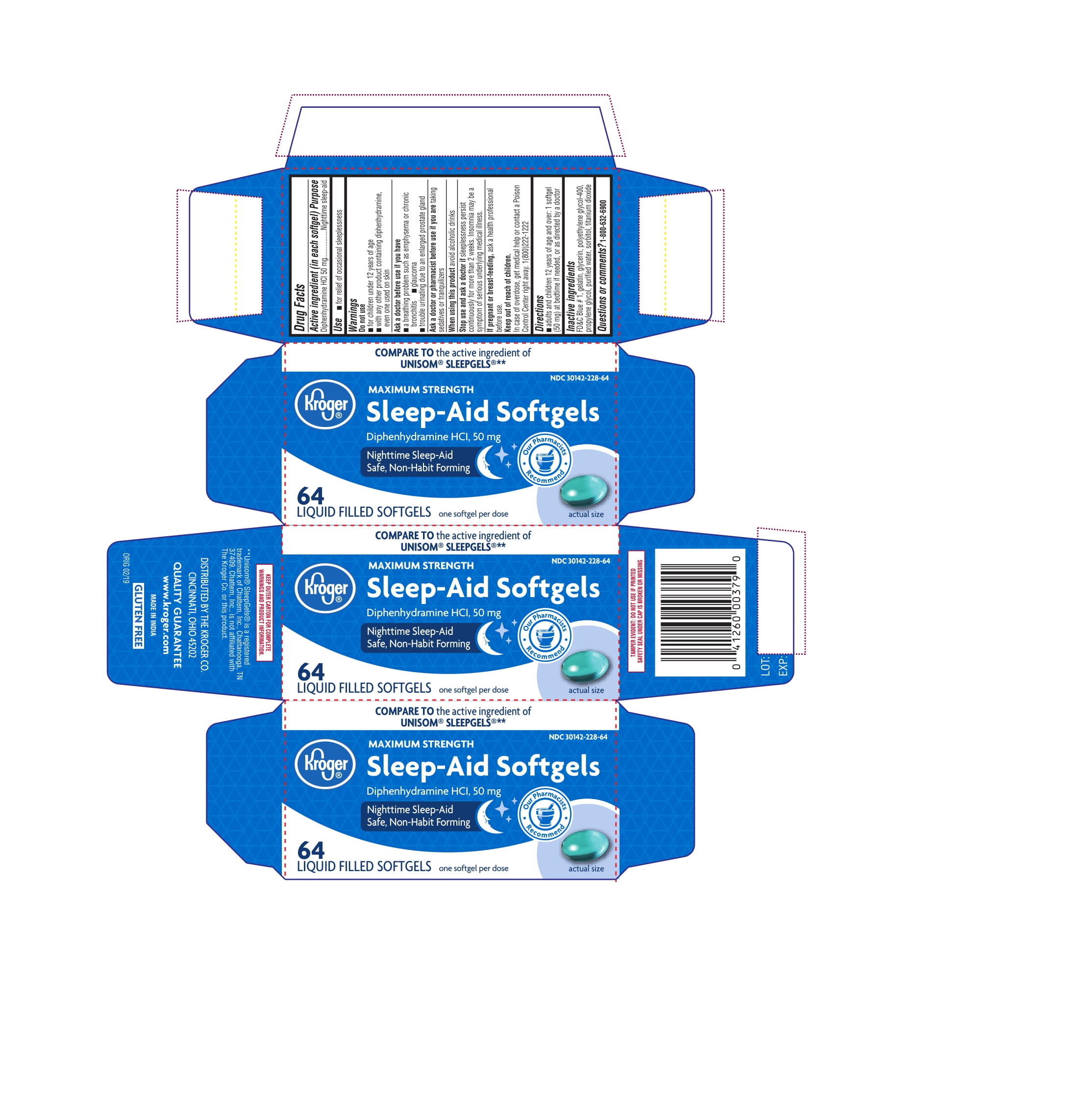 DRUG LABEL: MAXIMUM STRENGTH SLEEP AID
NDC: 30142-228 | Form: CAPSULE, GELATIN COATED
Manufacturer: KROGER COMPANY
Category: otc | Type: HUMAN OTC DRUG LABEL
Date: 20221123

ACTIVE INGREDIENTS: DIPHENHYDRAMINE HYDROCHLORIDE 50 mg/1 1
INACTIVE INGREDIENTS: SORBITOL; TITANIUM DIOXIDE; WATER; FD&C BLUE NO. 1; GELATIN; GLYCERIN; POLYETHYLENE GLYCOL 400; PROPYLENE GLYCOL

Kroger® MAXIMUM STRENGTH Sleep Aid Softgels

Drug Facts

Active ingredient (in each softgel)

Diphenhydramine HCl 50 mg

Purpose

Nighttime sleep-aid

Use

for the relief of occasional sleeplessness

Warnings

Do not use

- for children under 12 years of age
- with any other product containing diphenhydramine, even one used on skin

Ask a doctor before use if you have

- a breathing problem such as emphysema or chronic bronchitis
- glaucoma
- trouble urinating due to an enlarged prostate gland

Ask a doctor or pharmacist before use if you are taking sedatives or tranquilizers

When using this product avoid alcoholic drinks

Stop use and ask a doctor if

sleeplessness persist continuosly for more than 2 weeks. Insomnia may be a symptom of serious underlying medical illness.

PREGNANCY OR BREAST FEEDING

If pregnant or breast-feeding, ask a health professional before use.

Keep out of reach of children.

In case of overdose, get medical help or contact a Poison Control Center right away. 1-800-222-1222

Directions

- adults and children 12 years of age and over: 1 softgel (50 mg) at bedtime, if needed, or as directed by a doctor

Inactive ingredients

FD&C Blue#1, gelatin, glycerin, polyethylene glycol-400, propylene glycol, sorbitol, titanium dioxide, water

Questions or comments?

1-800-632-6900

DISTRIBUTED BY THE KROGER CO.
CINCINNATI, OHIO 45202

GLUTEN FREE

PRINCIPAL DISPLAY PANEL

COMPARE TO the active ingredient of
UNISOM® SLEEPGELS®**

NDC 30142-228-32

NDC 30142-228-40

NDC 30142-228-64

Kroger®

Sleep-Aid Softgels
MAXIMUM STRENGTH

Diphenhydramine HCI 50 mg

Nighttime Sleep Aid
Safe, Non-Habit Forming

32/40/64
LIQUID FILLED SOFTGELS one softgel per dose

actual size

**Unisom® SleepGels® is a registered trademark
of Chattem, Inc., Chattanooga, TN 37409.
Chattem, Inc., is not affiliated with The Kroger Co.
or this product.